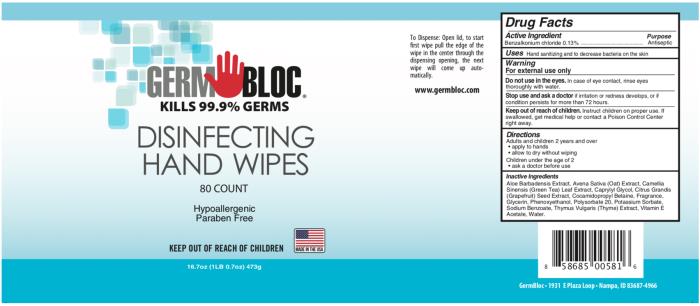 DRUG LABEL: Germ Bloc Disinfecting Hand Wipes
NDC: 69243-1110 | Form: CLOTH
Manufacturer: Willspeed Technologies LLC
Category: otc | Type: HUMAN OTC DRUG LABEL
Date: 20220114

ACTIVE INGREDIENTS: BENZALKONIUM CHLORIDE 0.0013 g/1 mL
INACTIVE INGREDIENTS: ALOE VERA LEAF; AVENA SATIVA LEAF; GREEN TEA LEAF; CAPRYLYL GLYCOL; CITRUS MAXIMA SEED; COCAMIDOPROPYL BETAINE; GLYCERIN; PHENOXYETHANOL; POLYSORBATE 20; POTASSIUM SORBATE; SODIUM BENZOATE; THYME; .ALPHA.-TOCOPHEROL ACETATE; WATER

Germ Bloc Disinfecting Hand Wipes

Drug Facts

Active Ingredients

Benzalkonium chloride 0.13%

Purpose

Antiseptic

Uses

For hand sanitizing. To decrease bacteria on the skin.

Warnings

For external use only.

Do not use

in the eyes.

In case of eye contact, rinse eyes thoroughly with water.

Stop use and ask a doctor

if irritation or redness develops or if condition persists more than 72 hours.

Keep out of reach of children.

Instruct children on proper use. If swallowed, get medical help or contact a Poison Control Center right away.

Directions

Adults and children 2 years and over

- apply to hands

- allow to dry without wiping

Children under the age of 2

- ask doctor before use

Inactive Ingredients

Aloe Barbadensis Extract, Avena Sativa (Oat) Extract, Camellia Sinensis (Green Tea) Leaf Extract, Caprylol Glycol, Citrus Grandis (Grapefruit) Seed Extract, Cocamidopropyl Betaine, Fragrance, Glycerin, Phenoxyethanol, Polysorbate 20, Potassium Sorbate, Sodium Benzoate, Thymus Vulgaris (Thyme) Extract, Vitamin E Acetate, Water.

PRINCIPAL DISPLAY PANEL

Alcohol-Free Formula
GERM BLOCTM
Kills 99.9% of Germs
Disinfecting Hand Wipes
80 Count

Hypoallergenic Paraben Free

Keep Out Of Reach Of Children
16.7oz (1LB 0.7oz) 473g